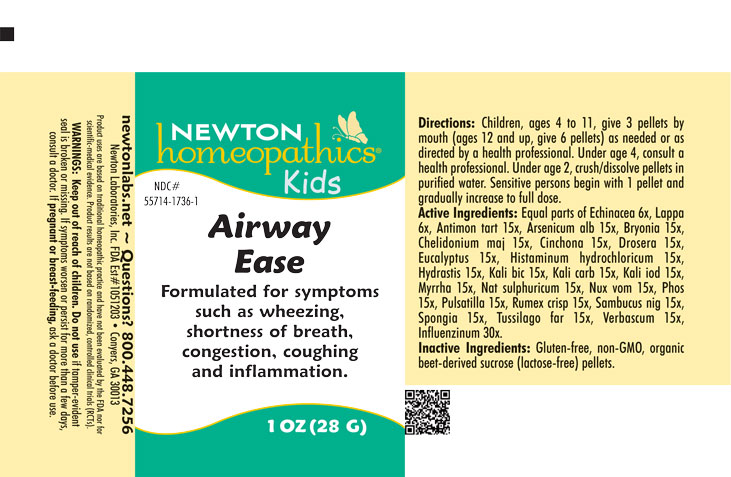 DRUG LABEL: Airway Ease
NDC: 55714-1736 | Form: PELLET
Manufacturer: Newton Laboratories, Inc.
Category: homeopathic | Type: HUMAN OTC DRUG LABEL
Date: 20250507

ACTIVE INGREDIENTS: SAMBUCUS NIGRA FLOWERING TOP 15 [hp_X]/1 g; INFLUENZA A VIRUS 30 [hp_X]/1 g; ANTIMONY POTASSIUM TARTRATE 15 [hp_X]/1 g; ARSENIC TRIOXIDE 15 [hp_X]/1 g; BRYONIA ALBA ROOT 15 [hp_X]/1 g; CHELIDONIUM MAJUS 15 [hp_X]/1 g; CINCHONA OFFICINALIS BARK 15 [hp_X]/1 g; DROSERA ANGLICA 15 [hp_X]/1 g; EUCALYPTUS GUM 15 [hp_X]/1 g; HISTAMINE DIHYDROCHLORIDE 15 [hp_X]/1 g; GOLDENSEAL 15 [hp_X]/1 g; POTASSIUM DICHROMATE 15 [hp_X]/1 g; POTASSIUM CARBONATE 15 [hp_X]/1 g; POTASSIUM IODIDE 15 [hp_X]/1 g; MYRRH 15 [hp_X]/1 g; SODIUM SULFATE 15 [hp_X]/1 g; STRYCHNOS NUX-VOMICA SEED 15 [hp_X]/1 g; PHOSPHORUS 15 [hp_X]/1 g; ANEMONE PULSATILLA 15 [hp_X]/1 g; RUMEX CRISPUS ROOT 15 [hp_X]/1 g; SPONGIA OFFICINALIS SKELETON, ROASTED 15 [hp_X]/1 g; TUSSILAGO FARFARA 15 [hp_X]/1 g; VERBASCUM THAPSUS 15 [hp_X]/1 g; ECHINACEA, UNSPECIFIED 6 [hp_X]/1 g; ARCTIUM LAPPA ROOT 6 [hp_X]/1 g; INFLUENZA B VIRUS 30 [hp_X]/1 g
INACTIVE INGREDIENTS: SUCROSE

Airway 1736P

OTC - KEEP OUT OF REACH OF CHILDREN SECTION

Keep out of reach of children.

OTC - PREGNANCY OR BREAST FEEDING SECTION

If pregnant or breast-feeding, ask a doctor before use.

WARNINGS SECTION

Warning: Keep out of reach of children. Do not use if tamper-evident seal is broken or missing. If symptoms worsen or persist for more than a few days, consult a doctor. If pregnant or breast-feeding, ask a doctor before use.

QUESTIONS SECTION

newtonlabs.net – Questions? 800.448.7256

Newton Laboratories, Inc. FDA Est # 1051203 - Conyers, GA 30013

INACTIVE INGREDIENT SECTION

Inactive Ingredients: Gluten-free, non-GMO, beet-derived sucrose (Lactose-free) pellets.

OTC - PURPOSE SECTION

Formulated for symptoms such as wheezing, shortness of breath, congestion, coughing and inflammation.

OTC - ACTIVE INGREDIENT SECTION

Equal parts of Echinacea 6x, Lappa 6x, Antimon. tart. 15x, Arsenicum alb. 15x, Bryonia 15x, Chelidonium maj. 15x, Cinchona 15x, Drosera 15x, Eucalyptus 15x, Histaminum hydrochloricum 15x, Hydrastis 15x, Kali bic. 15x, Kali carb. 15x, Kali iod. 15x, Myrrha 15x, Nat. sulphuricum 15x, Nux vom. 15x, Phos. 15x, Pulsatilla 15x, Rumex crisp. 15x, Sambucus nig. 15x, Spongia 15x, Tussilago far. 15x, Verbascum 15x ,Influenzinum 30x.

DOSAGE & ADMINISTRATION SECTION

Directions: Children, ages 4 to 11, give 3 pellets by mouth (ages 12 and up, give 6 pellets) as needed or as directed by a health professional. Under age 4, consult a health professional. Under age 2, crush/desolve pellets in purified water. Sensitive persons begin with 1 pellet and gradually increase to full dose.

INDICATIONS & USAGE SECTION

Formulated for symptoms such as wheezing, shortness of breath, congestion, coughing and inflammation.